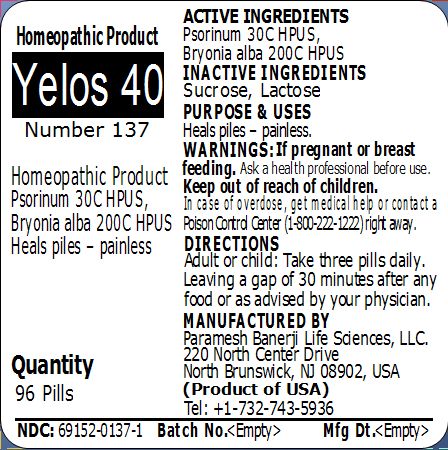 DRUG LABEL: Yelos 40 Number 137
NDC: 69152-0137 | Form: PELLET
Manufacturer: Paramesh Banerji Life Sciences LLC
Category: homeopathic | Type: HUMAN OTC DRUG LABEL
Date: 20150221

ACTIVE INGREDIENTS: SCABIES LESION LYSATE (HUMAN) 30 [hp_C]/1 1; BRYONIA ALBA ROOT 200 [hp_C]/1 1
INACTIVE INGREDIENTS: SUCROSE; LACTOSE

Active Ingredients

Psorinum 30C HPUS, Bryonia alba 200C HPUS

Inactive Ingredients

Sucrose, Lactose

Purpose

Heals piles – painless

Uses

Heals piles – painless

Warnings

If pregnant or breast feeding ask a health professional before use.

Keep out of reach of children. In case of overdose, get medical help or contact a Poison Control Center (1-800-222-1222) right away.

Direction

Adult or child: Take three pills daily. Leaving a gap of 30 minutes after any food or as advised by your physician.

Manufactured by

Paramesh Banerji Life Sciences, LLC

220 North Center Drive

North Brunswick, NJ 08902, USA

Product of USA

Tel: +1-732-743-5936

Principal Display Panel

Homeopathic Product

Yelos 40

Number 137

Homeopathic Product

Psorinum 30C HPUS, Bryonia alba 200C HPUS

Heals piles – painless

Quantity

96 Pills